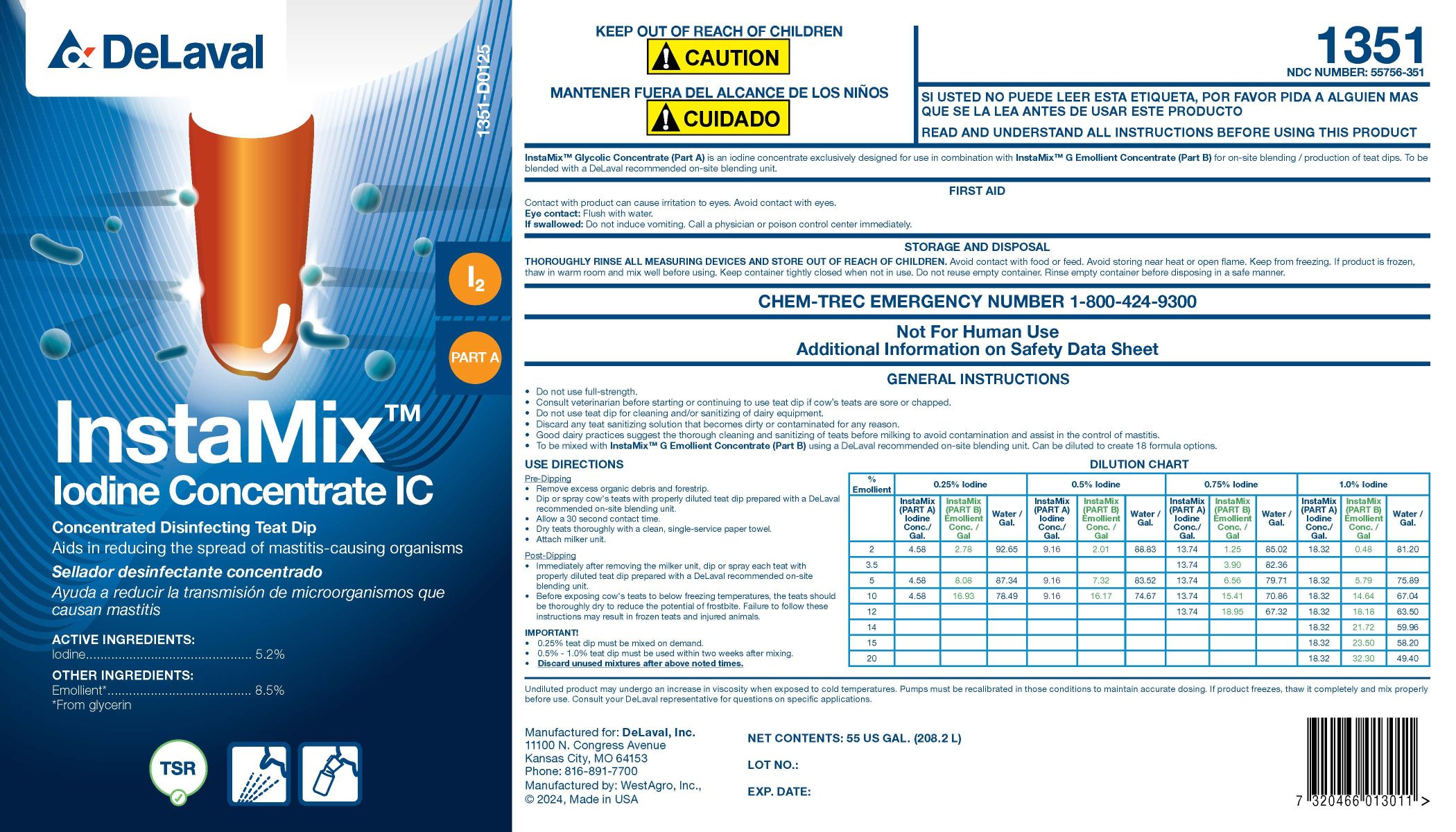 DRUG LABEL: InstaMix Iodine Concentrate IC
NDC: 55756-351 | Form: CONCENTRATE
Manufacturer: DeLaval Inc.
Category: animal | Type: OTC ANIMAL DRUG LABEL
Date: 20250303

ACTIVE INGREDIENTS: IODINE 52 g/1 L
INACTIVE INGREDIENTS: GLYCERIN; SODIUM HYDROXIDE; ANHYDROUS CITRIC ACID; POLOXAMER 335; DOCUSATE SODIUM; WATER

InstaMixTM
Iodine Concentrate IC

PURPOSE

Concentrated Disinfecting Teat Dip

Aids in reducing the spread of mastitis-causing organisms

ACTIVE INGREDIENTS:

Iodine............................ 5.2%

OTHER INGREDIENTS:

Emollient* ............................ 8.5%

*From glycerin

I²

PART A

KEEP OUT OF REACH OF CHILDREN

! CAUTION

WARNINGS

READ AND UNDERSTAND ALL INSTRUCTIONS BEFORE USING THIS PRODUCT

FIRST AID

Contact with product can cause irritation to eyes. Avoid contact with eyes.

Eye Contact: Flush with water.

If swallowed: Do not induce vomiting. Call a physician or poison control center immediately.

INDICATIONS AND USAGE

InstaMix™ Glycolic Concentrate (Part A) is an iodine concentrate exclusively designed for use in combination with InstaMix™ G Emollient Concentrate (Part B) for on-site blending / production of teat dips. To be blended with a DeLaval recommended on-site blending unit.

STORAGE AND DISPOSAL

THOROUGHLY RINSE ALL MEASURING DEVICES AND STORE OUT OF REACH OF CHILDREN. Avoid contact with food or feed. Avoid storing near heat or open flame. Keep from freezing. If product is frozen, thaw in warm room and mix well before using. Keep container tightly closed when not in use. Do not reuse empty container. Rinse empty container before disposing in a safe manner.

GENERAL INSTRUCTIONS

- Do not use full-strength.
- Consult veterinarian before starting or continuing to use teat dip if cow's teats are sore or chapped.
- Do not use teat dip for cleaning and/or sanitizing of dairy equipment.
- Discard any teat sanitizing solution that becomes dirty or contaminated for any reason.
- Good dairy practices suggest the thorough cleaning and sanitizing of teats before milking to avoid contamination and assist in the control of mastitis.
- To be mixed with InstaMix™ G Emollient Concentrate (Part B) using a DeLaval recommended on-site blending unit. Can be diluted to create 18 formula options.

USE DIRECTIONS

Pre-Dipping

- Remove excess organic debris and forestrip.
- Dip or spray cow's teats with properly diluted teat dip prepared with the DeLaval recommended on-site blending unit.
- Allow a 30 second contact time.
- Dry teats thoroughly with a clean, single-service paper towel.
- Attach milker unit.

Post-Dipping

- Immediately after removing the milker unit, dip or spray each teat with properly diluted teat dip prepared with a DeLaval recommended on-site blending unit.
- Before exposing cow's teats to below freezing temperatures, the teats should be thoroughly dry to reduce the potential of frostbite. Failure to follow these instructions may result in frozen teats and injured animals.

DILUTION CHART
% Emollient | 0.25% Iodine | 0.25% Iodine | 0.25 % Iodine | 0.5% Iodine | 0.5% Iodine | 0.5% Iodine | 0.75% Iodine | 0.75 % Iodine | 0.75% Iodine | 1.0% Iodine | 1.0% Iodine | 1.0% Iodine
 | InstaMix (PART A) Iodine Conc./Gal. | InstaMix (PART B) Emollient Conc./Gal | Water/Gal. | InstaMix (PART A) Iodine Conc./Gal. | InstaMix (PART B) Emollient Conc./Gal | Water/Gal. | InstaMix (PART A) Iodine Conc./Gal. | InstaMix (PART B) Emollient Conc./Gal | Water/Gal. | InstaMix (PART A) Iodine Conc./Gal. | InstaMix (PART B) Emollient Conc./Gal | Water/Gal.
2 | 4.58 | 2.78 | 92.65 | 9.16 | 2.01 | 88.83 | 13.74 | 1.25 | 85.02 | 18.32 | 0.48 | 81.20
3.5 |  |  |  |  |  |  | 13.74 | 3.90 | 82.36
5 | 4.58 | 8.08 | 87.34 | 9.16 | 7.32 | 83.52 | 13.74 | 6.56 | 79.71 | 18.32 | 5.79 | 75.89
10 | 4.58 | 16.93 | 78.49 | 9.16 | 16.17 | 74.67 | 13.74 | 15.41 | 70.86 | 18.32 | 14.64 | 67.04
12 |  |  |  |  |  |  | 13.74 | 18.95 | 67.32 | 18.32 | 18.18 | 63.50
14 |  |  |  |  |  |  |  |  |  | 18.32 | 21.72 | 59.96
15 |  |  |  |  |  |  |  |  |  | 18.32 | 23.50 | 58.20
20 |  |  |  |  |  |  |  |  |  | 18.32 | 32.30 | 49.40

IMPORTANT!

- 0.25% teat dip must be mixed on demand.
- 0.5% - 1.0% teat dip must be used within two weeks after mixing.
- Discard unused mixtures after above noted times.

WARNINGS AND PRECAUTIONS

Undiluted product may undergo an increase in viscosity when exposed to cold temperatures. Pumps must be recalibrated in those conditions to maintain accurate dosing. If product freezes, thaw it completely and mix properly before use. Consult your DeLaval representative for questions on specific applications.

NET CONTENTS: US GAL. (L)

LOT NO.:

EXP. DATE:

Manufactured for: DeLaval, Inc.

11100 N. Congress Avenue

Kansas City, MO 64153

Phone: 816-891-7700

Manufactured by: WestAgro, Inc.,

© 2924, Made in USA

PACKAGE LABEL

Add image transcription here...